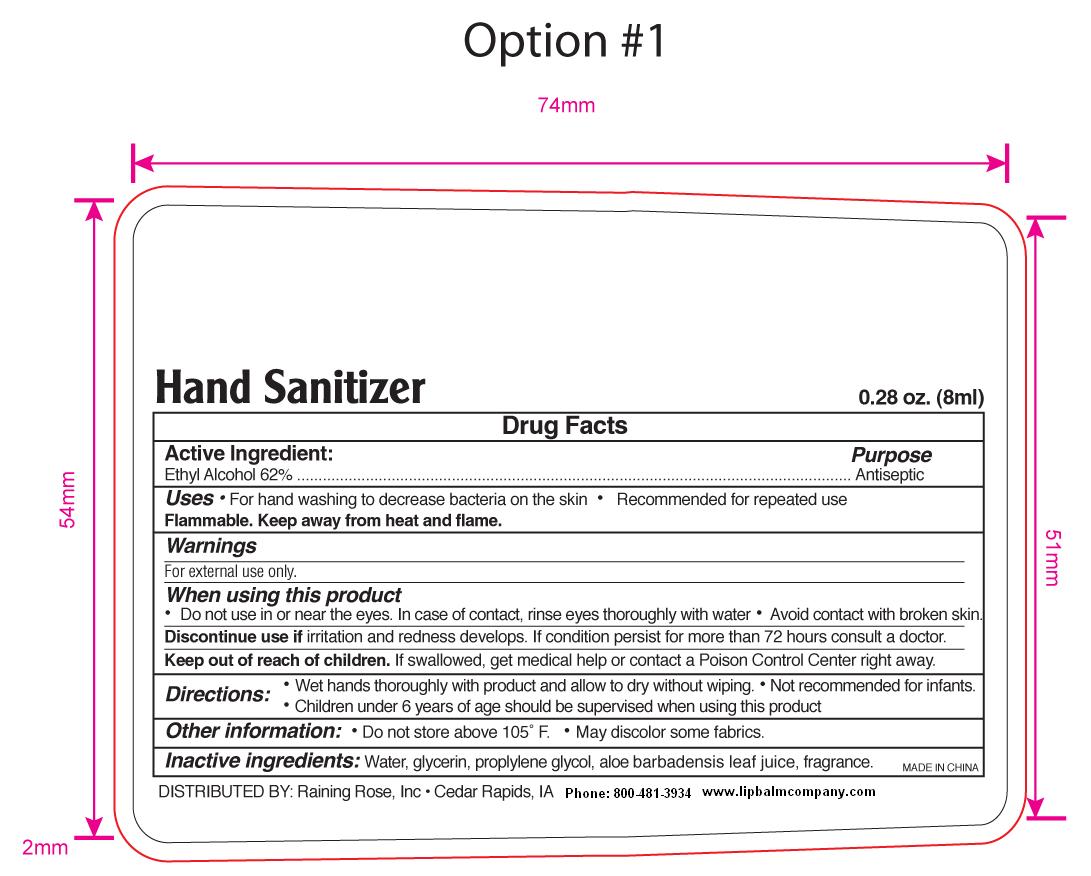 DRUG LABEL: Raining Rose Antiseptic Hand Sanitizer
                
NDC: 65692-1001 | Form: SPRAY
Manufacturer: Raining Rose, Inc.
Category: otc | Type: HUMAN OTC DRUG LABEL
Date: 20121130

ACTIVE INGREDIENTS: Alcohol 62 mL/100 mL
INACTIVE INGREDIENTS: WATER; GLYCERIN; PROPYLENE GLYCOL; ALOE VERA LEAF

Active ingredient
Ethyl Alcohol 62%

Purpose
Antiseptic

Uses
For hand washing to decrease bacteria on the skin
Recommended for repeated use
Flammable. Keep away from heat and flame.

Warnings
For external use only.

When using this product
Do not use in or near the eyes. In case of contact, rinse eyes thoroughly with water. Avoid contact with broken skin.

Discontinue Use
if irritation and redness develops. If condition persists for more than 72 hours consult a doctor.

Keep out of reach of children.
If swallowed get medical help or contact a Poison Control Center right away.

Directions
Wet hands thoroughly with product and allow to dry without wiping
Children under 6 of age should be supervised when using this product.
Not recommended for infants.
Other Information
Do not store above 105 degrees F.
May discolor some fabrics.

Inactive Ingredients
Water, glycerin, propylene glycol,

aloe barbadenis leaf Juice, fragrance